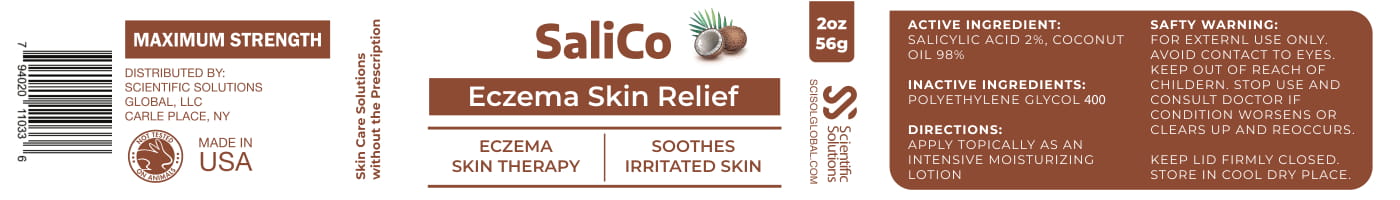 DRUG LABEL: SaliCo
NDC: 81376-304 | Form: LOTION
Manufacturer: SSG Ventures Inc
Category: otc | Type: HUMAN OTC DRUG LABEL
Date: 20210111

ACTIVE INGREDIENTS: SALICYLIC ACID 1 g/1 g
INACTIVE INGREDIENTS: COCONUT OIL; POLYETHYLENE GLYCOL 400

Salico

PACKAGE LABEL

Active Ingredient

SALICYLIC ACID 2%, COCONUT OIL 99.9%

Inactive Ingredients:

POLYETHYLENE GLYCOL 400

Directions:

APPLY TOPICALLY AS AN INTENSIVE MOISTURIZING LOTION

SAFETY WARNING:

FOR EXTERNAL USE ONLY:

AVOID CONTACT TO EYES.

KEEP OUT OF REACH OF CHILDREN.

STOP USE AND CONSULT DOCTOR IF CONDITION WORSENS OR CLEARS UP AN REOCCURS.

KEEP LID FIRMLY CLOSED.

STORE IN COOL DRY PLACE

PURPOSE

ECZEMA SKIN THERAPY

SOOTHES IRRITATED SKIN

KEEP OUT OF REACH OF CHILDREN

INDICATIONS AND USAGE

ECZEMA SKIN THERAPY

SOOTHES IRRITATED SKIN